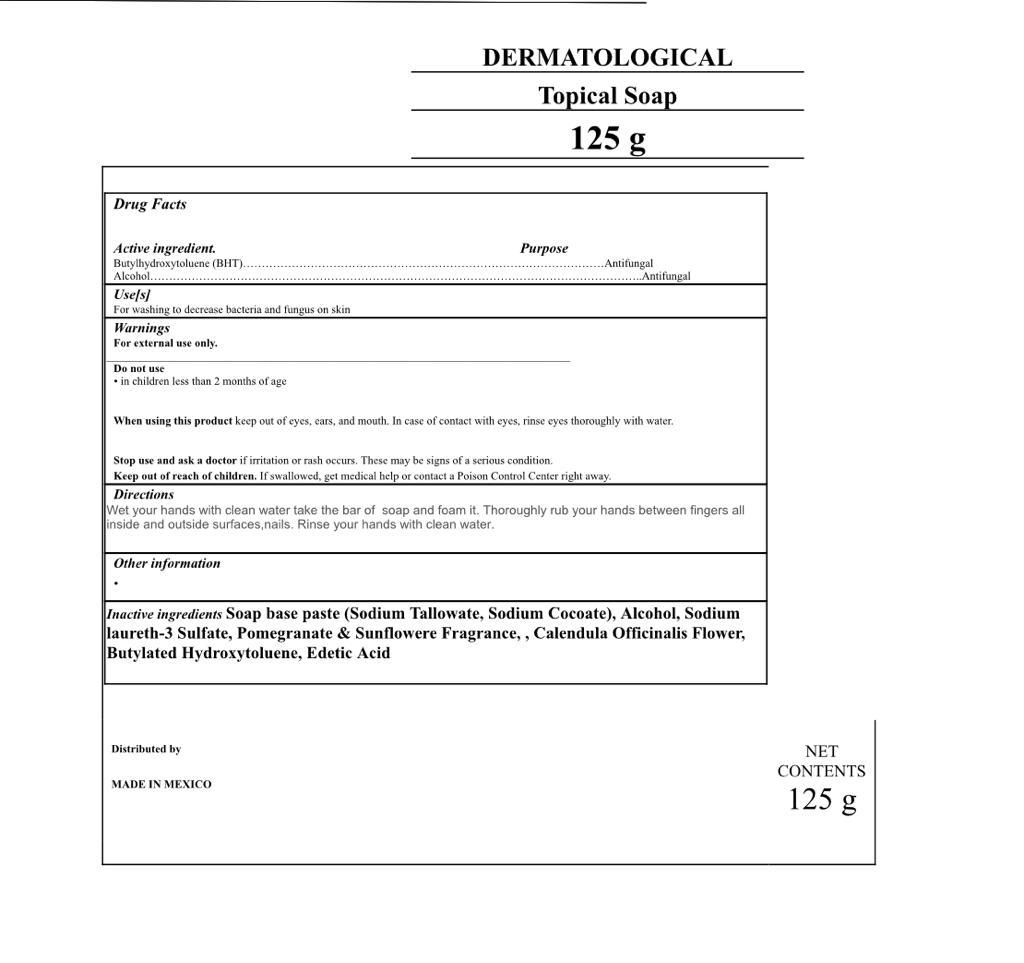 DRUG LABEL: DERMATOLOGICAL
NDC: 79577-7000 | Form: SOAP
Manufacturer: PROMAQUILA DE COCULA, S.A. DE C.V.
Category: otc | Type: HUMAN OTC DRUG LABEL
Date: 20230529

ACTIVE INGREDIENTS: ALCOHOL 0.001 g/1 g; BUTYLATED HYDROXYTOLUENE 0.001 g/1 g
INACTIVE INGREDIENTS: EDETIC ACID 0.001 g/1 g; SODIUM TALLOWATE, BEEF 0.8622 g/1 g; CALENDULA OFFICINALIS FLOWER 0.1 g/1 g; SODIUM LAURETH-3 SULFATE 0.194 g/1 g; SODIUM COCOATE 0.0957 g/1 g

DERMATOLOGICAL SOAP

ACTIVE INGREDIENT SECTION

ACTIVE INGREDIENT Butylhydroxytoluene (BHT) .10 %

ALCOHOL

PURPOSE

PURPOSE ANTIFUNGAL

DOSAGE AND ADMINISTRATION

DIRECTIONS

Wet your hands with clean water take the bar of soap and foam it. Thoroughly rub your hands between fingers all inside and outside surfaces,nails. Rinse your hands with clean water.

WARNINGS

WARNING

FOR EXTERNAL USE ONLY

WARNINGS AND PRECAUTIONS

When using this product keep out of eyes, ears, and mouth. In case of contact with eyes, rinse eyes thoroughly with water.

KEEP OUT OF REACH OF CHILDREN

STOP USE SECTION

Stop use and ask a doctor if irritation or rash occurs. These may be signs of a serious condition.

USE

Use[s]

For washing to decrease bacteria and fungus on skin

INACTIVE INGREDIENTS

Soap base paste (Sodium Tallowate, Beef, Sodium Cocoate)
Sodium laureth-3 sulfate

Pomegranate & Sunflower Fragrance

Calendula Officinalis Flower
Edetic Acid

WARNING SECTION

For external use only.